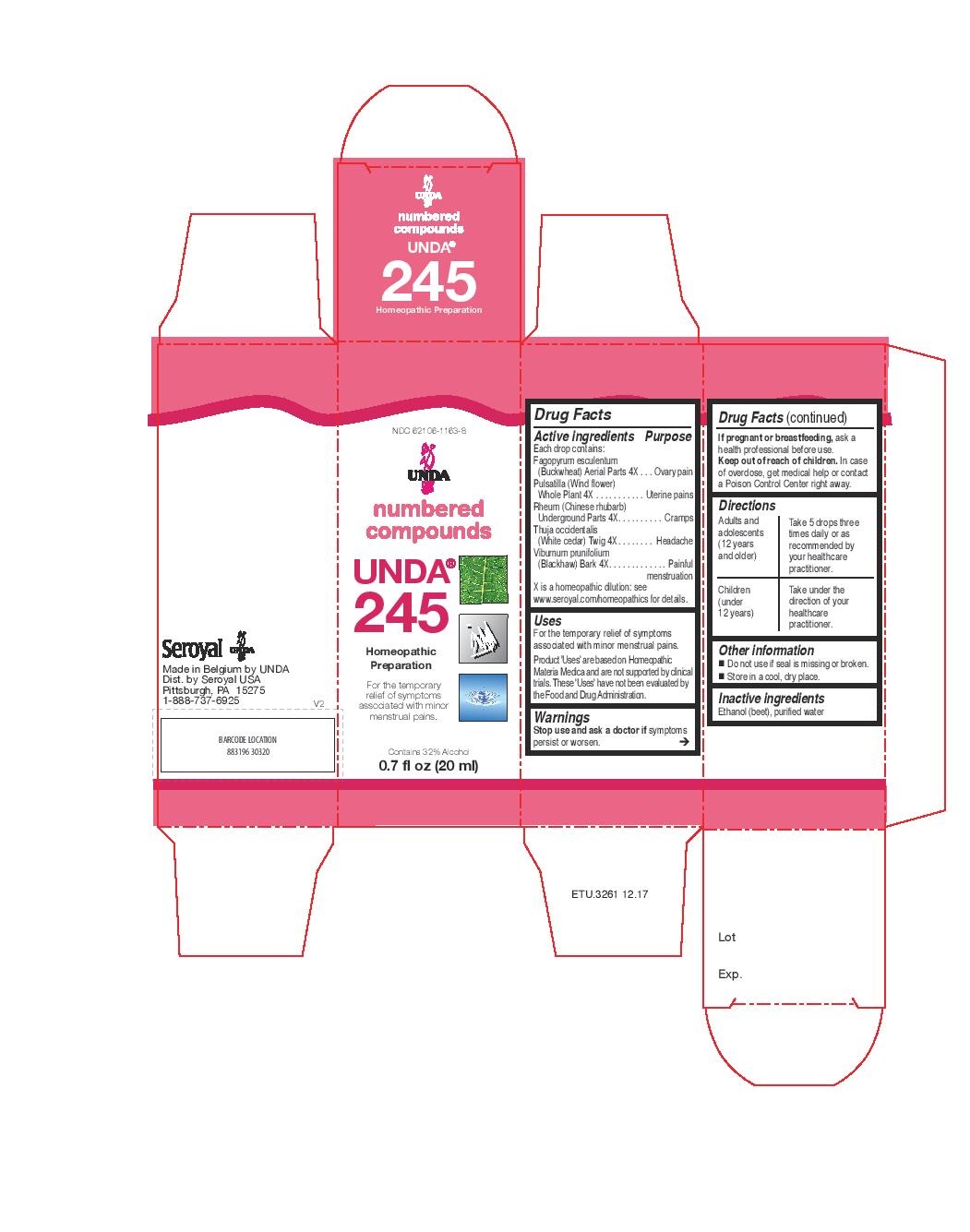 DRUG LABEL: Unda 245
NDC: 62106-1163 | Form: LIQUID
Manufacturer: Seroyal USA
Category: homeopathic | Type: HUMAN OTC DRUG LABEL
Date: 20221109

ACTIVE INGREDIENTS: RHEUM TANGUTICUM WHOLE 4 [hp_X]/20 mL; VIBURNUM PRUNIFOLIUM BARK 4 [hp_X]/20 mL; THUJA OCCIDENTALIS LEAFY TWIG 4 [hp_X]/20 mL; PULSATILLA VULGARIS 4 [hp_X]/20 mL; FAGOPYRUM ESCULENTUM 4 [hp_X]/20 mL
INACTIVE INGREDIENTS: ALCOHOL; WATER

Unda 245

Active ingredients
Each drop contains:
Fagopyrum esculentum (Buckwheat) Aerial Parts 4X
Pulsatilla (Wind flower) Whole Plant 4X
Rheum (Chinese rhubarb) Underground Parts 4X
Thuja occidentalis (White cedar) Twig 4X
Viburnum prunifolium (Blackhaw) Bark 4X

Uses
For the temporary relief of symptoms associated with minor menstrual pains.

Warnings
Stop use and ask a doctor if symptoms
persist or worsen.
If pregnant or breastfeeding, ask a
health professional before use.
Keep out of reach of children. In case
of overdose, get medical help or contact
a Poison Control Center right away.

PREGNANCY OR BREAST FEEDING

If pregnant or breastfeeding, ask a health professional before use.

Keep out of reach of children.

OVERDOSAGE

In case of overdose, get medical help or contact a
Poison Control Center right away.

Inactive ingredients
Ethanol (beet), purified water

Other information
Do not use if seal is missing or broken.
Store in a cool, dry place.

Directions
Adults and adolescents (12 years and older)

Take 5 drops three times daily or as
recommended by your healthcare practitioner.
Children (under 12 years)
Take under the direction of your
healthcare practitioner.

Uses
For the temporary relief of symptoms associated with minor menstrual pains.

Directions
Adults and adolescents (12 years and older)

Take 5 drops three times daily or as recommended by your healthcare practitioner.
Children (under 12 years)
Take under the direction of your healthcare practitioner.

PACKAGE LABEL

NDC 62106-1163-8

UNDA

numbered compounds

UNDA 245

Homeopathic Preparation

For the temporary relief of symptoms
associated with minor menstrual pains.

Contains 32% Alcohol
0.7 fl oz (20 mL)